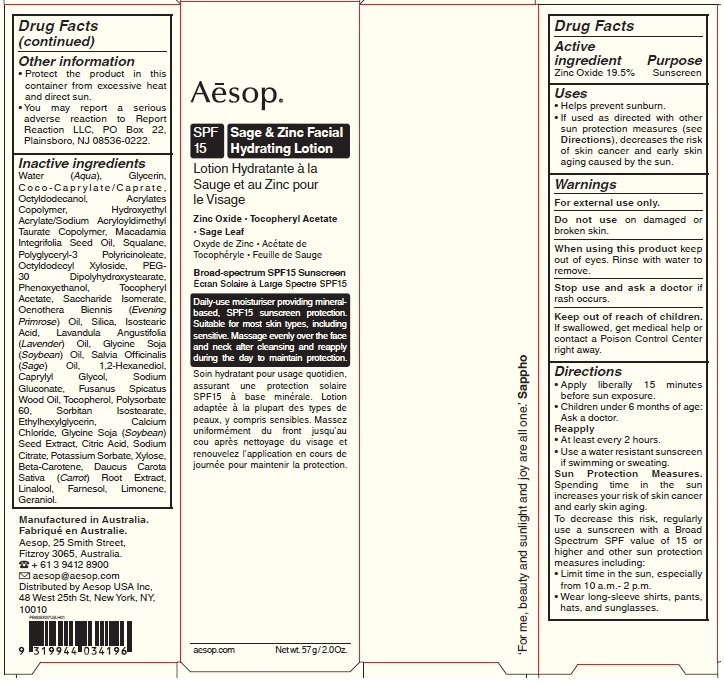 DRUG LABEL: Sage and Zinc Facial Hydrating SPF15
NDC: 76293-372 | Form: LOTION
Manufacturer: Emeis Cosmetics Pty Ltd
Category: otc | Type: HUMAN OTC DRUG LABEL
Date: 20251218

ACTIVE INGREDIENTS: ZINC OXIDE 195 mg/1 g
INACTIVE INGREDIENTS: CALCIUM CHLORIDE; SOYBEAN; SODIUM CITRATE; POTASSIUM SORBATE; XYLOSE; CARROT; SILICON DIOXIDE; TOCOPHEROL; HYDROXYETHYL ACRYLATE/SODIUM ACRYLOYLDIMETHYL TAURATE COPOLYMER (45000 MPA.S AT 1%); MACADAMIA OIL; POLYGLYCERYL-3 PENTARICINOLEATE; EVENING PRIMROSE OIL; SAGE OIL; SORBITAN ISOSTEARATE; COCO-CAPRYLATE/CAPRATE; CAPRYLYL GLYCOL; SODIUM GLUCONATE; SANTALUM SPICATUM OIL; POLYSORBATE 60; GERANIOL; LUVISET 360; BETA CAROTENE; LINALOOL, (+/-)-; FARNESOL; LIMONENE, (+)-; SACCHARIDE ISOMERATE; PEG-30 DIPOLYHYDROXYSTEARATE; PHENOXYETHANOL; .ALPHA.-TOCOPHEROL ACETATE; SOYBEAN OIL; 1,2-HEXANEDIOL; LAVENDER OIL; ETHYLHEXYLGLYCERIN; SQUALANE; OCTYLDODECYL XYLOSIDE; ISOSTEARIC ACID; CITRIC ACID MONOHYDRATE; OCTYLDODECANOL; WATER; GLYCERIN

Sage & Zinc Facial Hydrating Lotion SPF15

Active ingredient

Zinc Oxide 19.5%

Purpose

Sunscreen

Uses

- Helps prevent sunburn.
- If used as directed with other sun protection measures (see Directions), decreases the risk of skin cancer and early skin aging caused by the sun.

Warnings

For external use only.

Do not use

on damaged or broken skin.

When using this product

keep out of eyes. Rinse with water to remove.

Stop use and ask a doctor

if rash occurs.

Keep out of reach of children.

If swallowed, get medical help or contact a Poison Control Center right away.

Directions

- Apply liberally 15 minutes before sun exposure.
- Children under 6 months of age: Ask a doctor.
- Reapply:
- At least every 2 hours.
- Use a water resistant sunscreen if swimming or sweating.
- Sun Protection Measures. Spending time in the sun increases risk of skin cancer and early skin aging. To decrease this risk, regularly use a sunscreen with a Broad Spectrum SPF value of 15 or higher and other sun protection measures including:
- Limit time in the sun, especially from 10 a.m. - 2 p.m..
- Wear long-sleeve shirts, pants, hats and sunglasses.

Other information

- Protect the product in this container from excessive heat and direct sun.
- You may report a serious adverse reaction to Report Reaction LLC, PO Box 22, Plainsboro, NJ 08536-0222

Inactive ingredients

Water (Aqua), Glycerin, Coco-Caprylate/Caprate, Octyldodecanol, Acrylates Copolymer, Hydroxyethyl Acrylate/Sodium Acryloyldimethyl Taurate Copolymer, Macadamia Integrifolia Seed Oil, Squalane, Polyglyceryl-3 Polyricinoleate, Octyldodecyl Xyloside, PEG-30 Dipolyhydroxystearate, Phenoxyethanol, Tocopheryl Acetate, Saccharide Isomerate, Oenothera Biennis (Evening Primrose) Oil, Silica, Isostearic Acid, Lavandula Angustifolia (Lavender) Oil, Glycine Soja (Soybean) Oil, Salvia Officinalis (Sage) Oil, 1,2-Hexanediol, Caprylyl Glycol, Sodium Gluconate, Fusanus Spicatus Wood Oil, Tocopherol, Polysorbate 60, Sorbitan Isostearate, Ethylhexylglycerin, Calcium Chloride, Glycine Soja (Soybean) Seed Extract, Citric Acid, Sodium Citrate, Potassium Sorbate, Xylose, Beta-Carotene, Daucus Carota Sativa (Carrot) Root Extract, Linalool, Farnesol, Limonene, Geraniol.

Company Information

Manufactured in Australia.

Aesop, 25 Smith Street,

Fitzroy 3065, Australia.

+61 3 9412 8900

aesop@aesop.com

Distributed by Aesop USA Inc,

48 West 25th St. New York, NY,

10010

Product Packaging

Aesop.

SPF 15 Sage & Zinc Facial Hydrating Lotion

Zinc Oxide

Tocopheryl Acetate

Sage Leaf

Broad-spectrum SPF15 Sunscreen

Daily-use moisturiser providing mineral-based, SPF15 sunscreen protection. Suitable for most skin types, including sensitive. Massage evenly over the face and neck after cleansing and reapply during the day to maintain protection

aesop.com

Net wt. 57 g/2.0Oz.